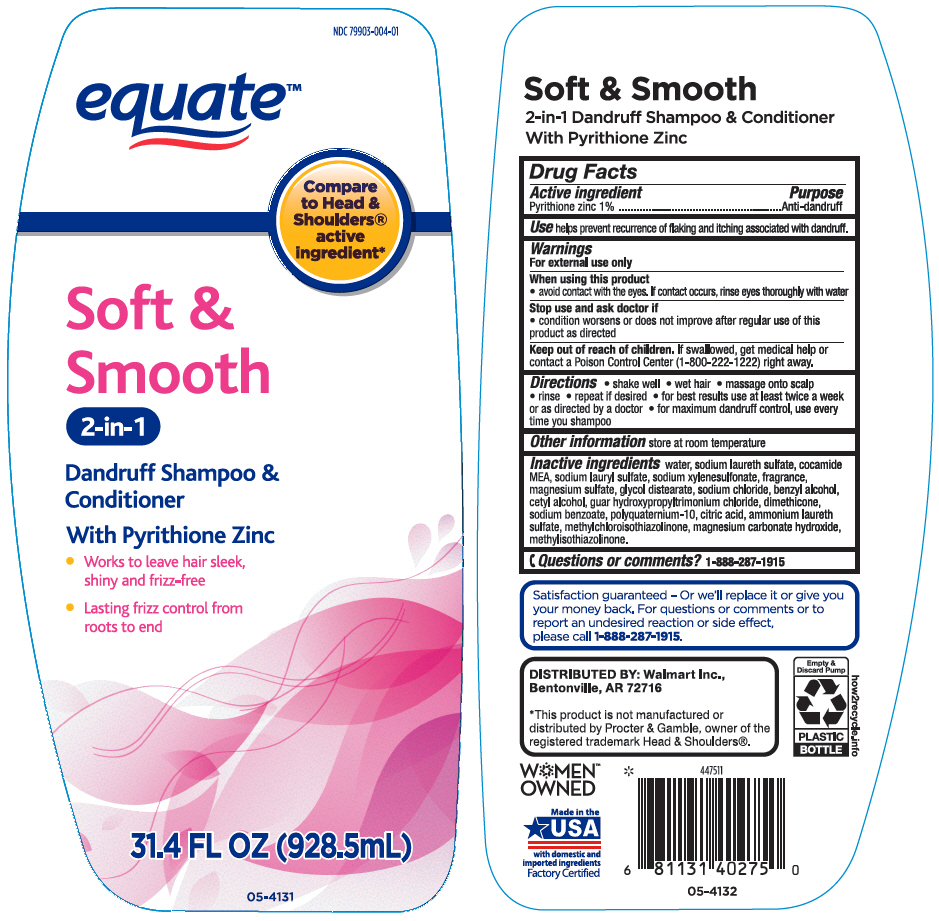 DRUG LABEL: Equate Soft and Smooth 2 in 1 Dandruff SH and COND
NDC: 79903-004 | Form: SHAMPOO
Manufacturer: Wal-Mart Stores, Inc.
Category: otc | Type: HUMAN OTC DRUG LABEL
Date: 20250110

ACTIVE INGREDIENTS: Pyrithione Zinc 10 mg/1 mL
INACTIVE INGREDIENTS: Water; SODIUM LAURETH-3 SULFATE; COCO MONOETHANOLAMIDE; Sodium Lauryl Sulfate; SODIUM XYLENESULFONATE; MAGNESIUM SULFATE, UNSPECIFIED FORM; Glycol Distearate; Sodium Chloride; Benzyl Alcohol; Cetyl Alcohol; GUAR HYDROXYPROPYLTRIMONIUM CHLORIDE; Dimethicone; Sodium Benzoate; POLYQUATERNIUM-10 (30000 MPA.S AT 2%); CITRIC ACID MONOHYDRATE; Methylchloroisothiazolinone; Magnesium Carbonate Hydroxide; Methylisothiazolinone

Equate™ Soft & Smooth 2 in 1 Dandruff SH & COND
Anti-Dandruff

Drug Facts

Active ingredient

Pyrithione Zinc 1%

Purpose

Anti-dandruff

Use

helps prevent recurrence of flaking and itching associated with dandruff.

Warnings

For external use only

When using this product

- avoid contact with the eyes. If contact occurs, rinse eyes thoroughly with water

Stop use and ask a doctor if

- condition worsens or does not improve after regular use of this product as directed

Keep out of reach of children. If swallowed, get medical help or contact a Poison Control Center (1-800-222-1222) right away.

Directions

- shake well
- wet hair
- massage onto scalp
- rinse
- repeat if desired
- for best results use at least twice a week or as directed by a doctor
- for maximum dandruff control, use every time you shampoo

Other information

store at room temperature

Inactive ingredients

water, sodium laureth sulfate, cocamide MEA, sodium lauryl sulfate, sodium xylenesulfonate, fragrance, magnesium sulfate, glycol distearate, sodium chloride, benzyl alcohol, cetyl alcohol, guar hydroxypropyltrimonium chloride, dimethicone, sodium benzoate, polyquaternium-10, citric acid, ammonium laureth sulfate, methylchloroisothiazolinone, magnesium carbonate hydroxide, methylisothiazolinone.

Questions or comments?

1-888-287-1915

DISTRIBUTED BY: Walmart Inc.,
Bentonville, AR 72716

PRINCIPAL DISPLAY PANEL - 928.5 mL Bottle Label

NDC 79903-004-01

equate™

Compare
to Head &
Shoulders®
active
ingredient*

Soft &
Smooth
2-in-1

Dandruff Shampoo &
Conditioner

With Pyrithione Zinc

- Works to leave hair sleek,
  shiny and frizz-free
- Lasting frizz control from
  roots to end

31.4 FL OZ (928.5mL)

05-4131